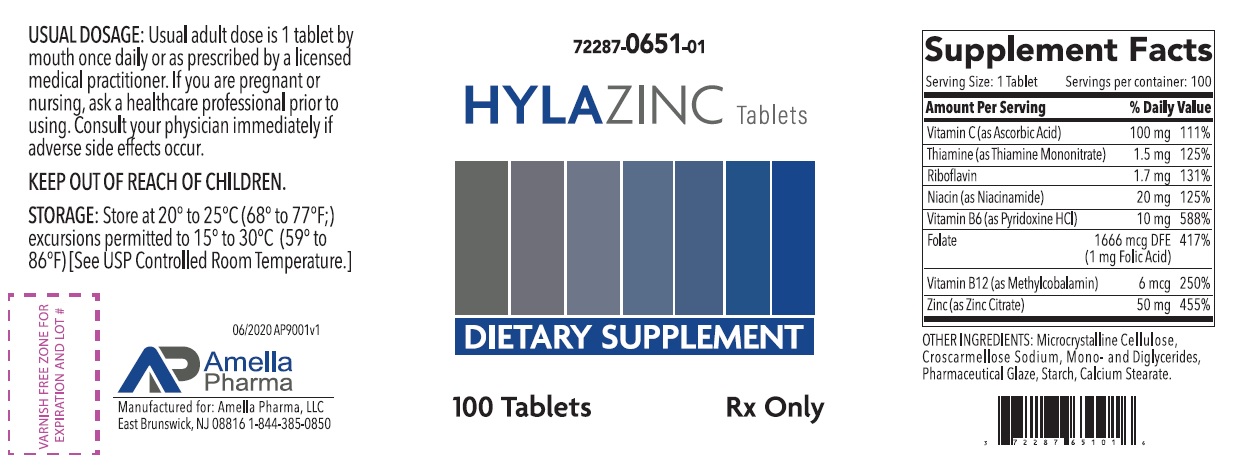 DRUG LABEL: HYLAZINC
NDC: 72287-651 | Form: TABLET, COATED
Manufacturer: AMELLA PHARMA, LLC
Category: other | Type: DIETARY SUPPLEMENT
Date: 20200924

ACTIVE INGREDIENTS: ZINC CITRATE 50 mg/1 1; ASCORBIC ACID 100 mg/1 1; THIAMINE MONONITRATE 1.5 mg/1 1; RIBOFLAVIN 1.7 mg/1 1; NIACINAMIDE 20 mg/1 1; PYRIDOXINE HYDROCHLORIDE 10 mg/1 1; FOLIC ACID 1 mg/1 1; METHYLCOBALAMIN 6 ug/1 1
INACTIVE INGREDIENTS: MICROCRYSTALLINE CELLULOSE; CROSCARMELLOSE SODIUM; GLYCERYL MONOSTEARATE; SHELLAC; STARCH, CORN; CALCIUM STEARATE

HYLAZINC

HYLAZINC Tablets Dietary Supplement Dispensed by Prescription†

Supplement Facts Serving Size: 1 Tablet Servings per container: 100
Amount Per Serving |  | % Daily Value
Zinc (as Zinc Citrate) | 50 mg | 455%
Vitamin C (as Ascorbic Acid) | 100 mg | 111%
Thiamine (as Thiamine Mononitrate) | 1.5 mg | 125%
Riboflavin | 1.7 mg | 131%
Niacin (as Niacinamide) | 20 mg | 125%
Vitamin B6 (as Pyridoxine HCl) | 10 mg | 588%
Folate | 1666 mcg DFE | 417%
 | (1 mg Folic Acid)
Vitamin B12 (as Methylcobalamin) | 6 mcg | 250%

OTHER INGREDIENTS: Microcrystalline Cellulose, Croscarmellose Sodium, Mono- and Diglycerides, Pharmaceutical Glaze, Starch, Calcium Stearate.

DESCRIPTION

HYLAZINC Tablets is an orally administered prescription vitamin formulation for the clinical dietary management of suboptimal nutritional status in patients where advanced folate supplementation is required and nutritional supplementation in physiologically stressful conditions for maintenance of good health is needed.

HYLAZINC is a small, round, yellow with yellow specks, clear-coated tablet, with debossed "A2" on one side.

PRECAUTIONS

CONTRAINDICATIONS

This product is contraindicated in patients with known hypersensitivity to any of the ingredients.

PRECAUTIONS

This product is contraindicated in patients with a known hypersensitivity to any of the ingredients.

HYLAZINC Tablets should only be used under the direction and supervision of a licensed medical practitioner. Use with caution in patients that may have a medical condition, are pregnant, lactating, trying to conceive, under the age of 18, or taking medications.

Folic acid supplementation may obscure pernicious anemia, in that hematologic remission can occur while neurological manifestations progress.

Keep out of reach of children.

Pregnancy and Lactation:
HYLAZINC Tablets is not intended for use in pregnant or lactating patients.

ADVERSE REACTIONS
Allergic sensitizations have been reported following oral administration of folic acid. Consult your physician immediately if adverse side effects occur.

DOSAGE AND ADMINISTRATION

Usual adult dose is 1 tablet by mouth once or twice daily or as prescribed by a licensed medical practitioner.

HOW SUPPLIED HEALTH CLAIM:

HYLAZINC Tablets are supplied as a small, round, yellow with yellow specks, clear-coated tablet, with debossed "A2" on one side.

HYLAZINC Tablets is available as the following:
72287-0651-01* 100ct bottle

Store at 20° to 25°C (68° to 77°F; excursions permitted to 15° to 30°C (59° to 86°F) [See USP Controlled Room Temperature]

Manufactured for:
Amella Pharma, LLC
E Brunswick, NJ 08816

Call your doctor for medical advice about side effects. You may report side effects to Amella Pharma, LLC at 1-844-385-0850.

Issued: 09/2020 AP9002v1

*Amella Pharma does not represent these product codes to be National Drug Codes (NDC). Product codes are formatted according to standard industry practice, to meet the formatting requirement by pedigree reporting and supply-chain control including pharmacies.

† This product is a prescription-folate with or without other dietary ingredients that – due to increased folate levels increased risk associated with masking of B12 deficiency (pernicious anemia) requires administration under the care of a licensed medical practitioner (61 FR 8760). The most appropriate way to ensure pedigree reporting consistent with these regulatory guidelines and safety monitoring is to dispense this product only by prescription (Rx). This is not an Orange Book product. This product may be administered only under a physician’s supervision and all prescriptions using this product shall be pursuant to state statutes as applicable. The ingredients, indication or claims of this product are not to be construed to be drug claims.

1. Federal Register Notice of August 2, 1973 (38 FR 20750)
2. Federal Register Notice of October 17, 1980 (45 FR 69043, 69044)
3. Federal Register Notice of March 5, 1996 (61 FR 8760)